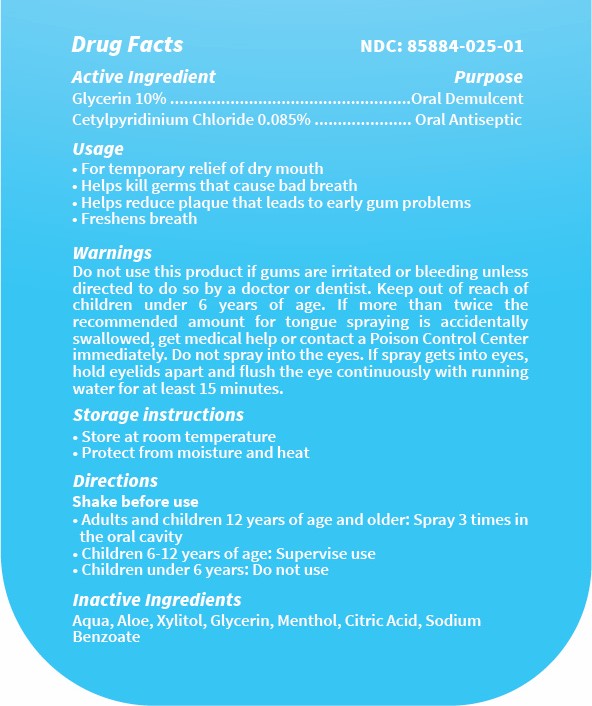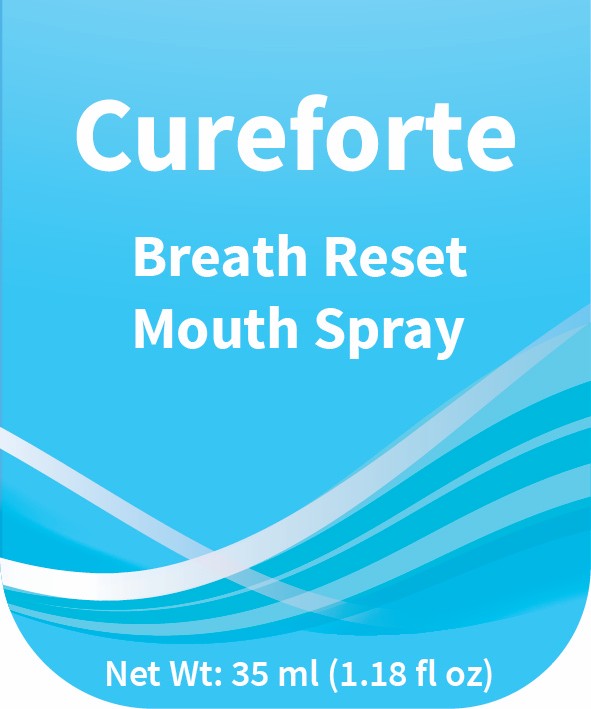 DRUG LABEL: Cureforte Breath Reset
NDC: 85884-025 | Form: SPRAY
Manufacturer: STEEL CITY HEALTH PRIVATE LIMITED
Category: otc | Type: HUMAN OTC DRUG LABEL
Date: 20250721

ACTIVE INGREDIENTS: CETYLPYRIDINIUM CHLORIDE 0.85 mg/1 mL; GLYCERIN 100 mg/1 mL
INACTIVE INGREDIENTS: ALOE; AQUA; SODIUM BENZOATE; XYLITOL; MENTHOL; CITRIC ACID MONOHYDRATE

INACTIVE INGREDIENT

Aqua, Xylitol, Aloe, Glycerin, Menthol, Sodium Benzoate, Citric acid

Usage:

For temporary relief of dry mouth
Helps kill germs that cause bad breath
Helps reduce plaque that leads to early gum problems
Freshens breath

Warnings:

For oral use only.Do not swallow. Not for children under 6 years of age Stop use and
ask a doctor if irritation or discomfort occurs. Keep out of reach of children

Purpose:

Glycerin – Temporarily relieves dry mouth
-Cetylpyridinium Chloride – Helps reduce germs that cause bad breath and plaque

KEEP OUT OF REACH OF CHILDREN

Warnings: For oral use only.Do not swallow. Not for children under 6 years of age Stop use and
ask a doctor if irritation or discomfort occurs. Keep out of reach of children